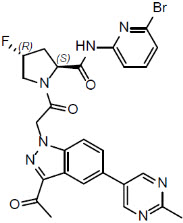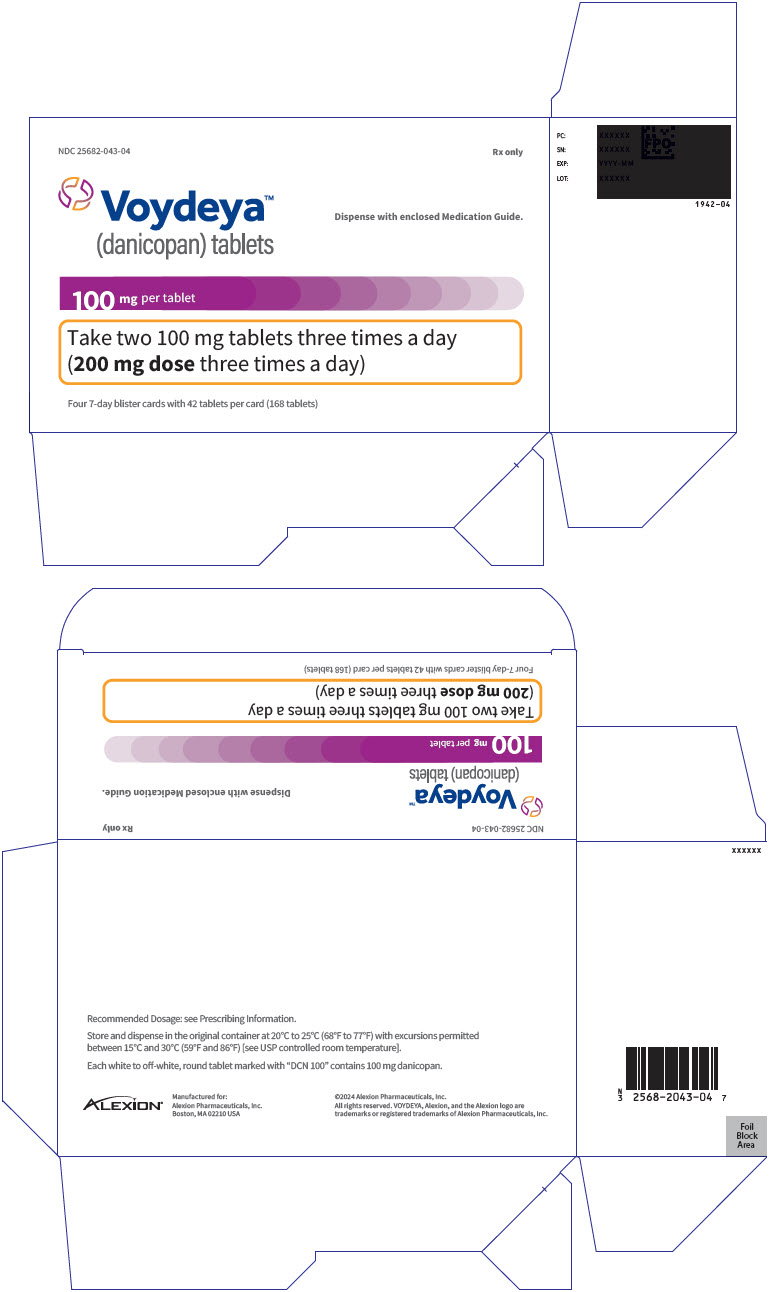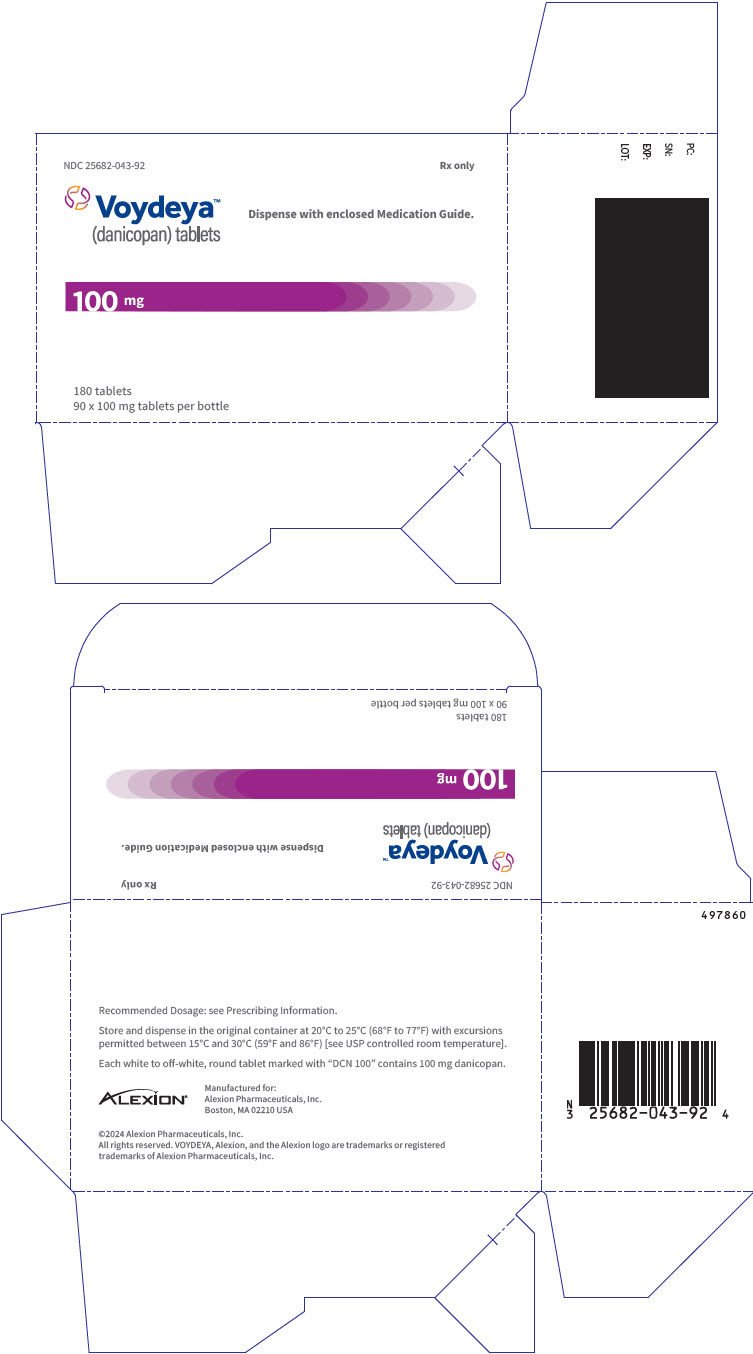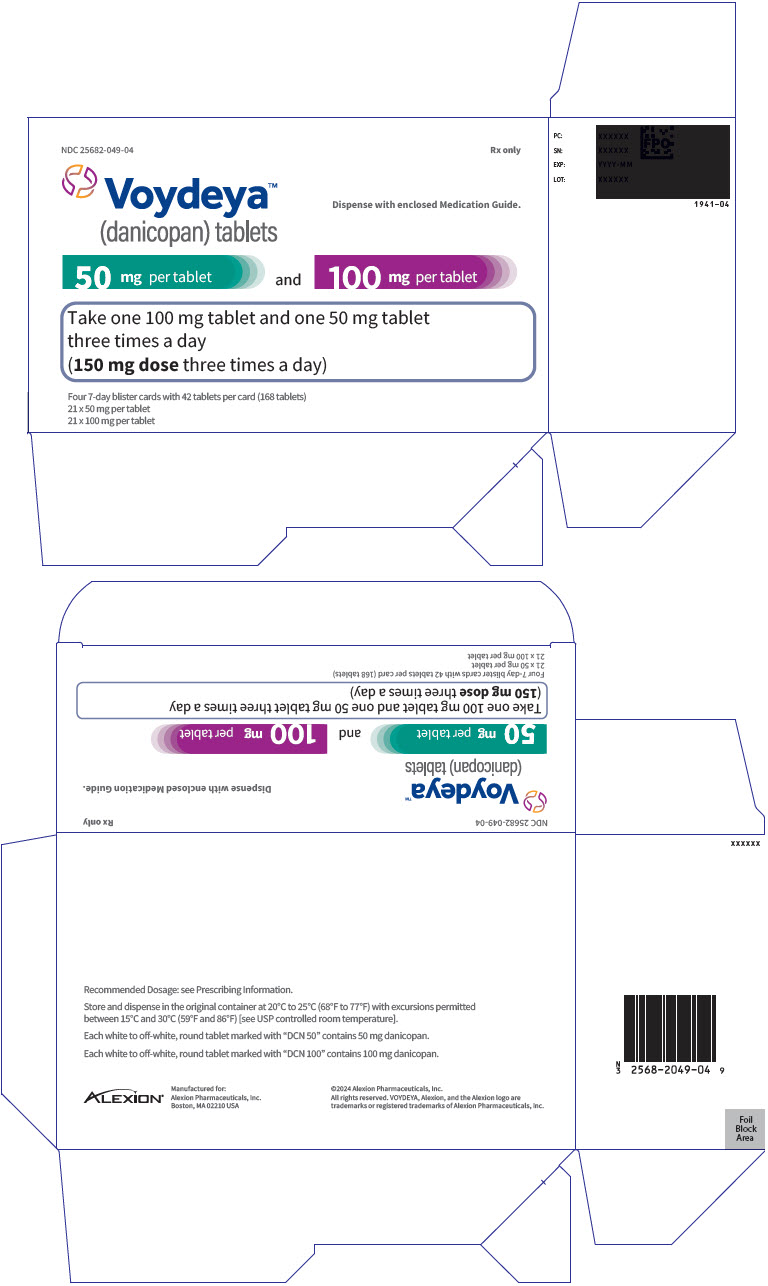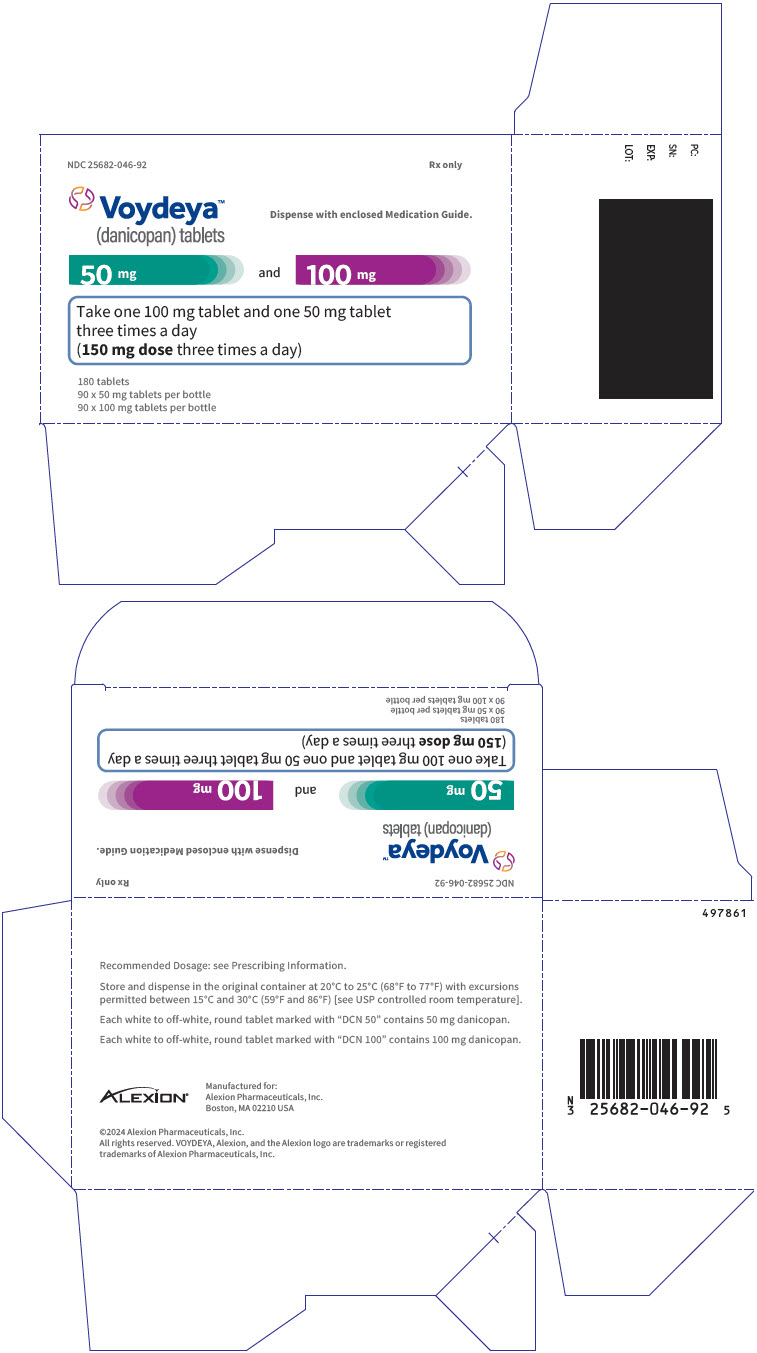 DRUG LABEL: Voydeya
NDC: 25682-043 | Form: TABLET, FILM COATED
Manufacturer: Alexion Pharmaceuticals Inc.
Category: prescription | Type: HUMAN PRESCRIPTION DRUG LABEL
Date: 20241206

ACTIVE INGREDIENTS: Danicopan 100 mg/1 1

HIGHLIGHTS OF PRESCRIBING INFORMATION

These highlights do not include all the information needed to use VOYDEYA safely and effectively. See full prescribing information for VOYDEYA.
VOYDEYA™ (danicopan) tablets, for oral use
Initial U.S. Approval: 2024

WARNING: SERIOUS INFECTIONS CAUSED BY ENCAPSULATED BACTERIA

See full prescribing information for complete boxed warning.

VOYDEYA increases the risk of serious and life-threatening infections, caused by encapsulated bacteria, including Neisseria meningitidis, Streptococcus pneumoniae, and Haemophilus influenzae type B (5.1).

- Complete or update vaccination for encapsulated bacteria at least 2 weeks prior to the first dose of VOYDEYA, unless the risks of delaying VOYDEYA outweigh the risk of developing a serious infection. Comply with the most current Advisory Committee on Immunization Practices (ACIP) recommendations for vaccinations against encapsulated bacteria in patients receiving a complement inhibitor (5.1).
- Patients receiving VOYDEYA are at increased risk for invasive disease caused by encapsulated bacteria, even if they develop antibodies following vaccination. Monitor patients for early signs and symptoms of serious infections and evaluate immediately if infection is suspected (5.1).

VOYDEYA is available only through a restricted program called VOYDEYA REMS (5.2).

1 INDICATIONS AND USAGE

VOYDEYA is a complement factor D inhibitor indicated as add-on therapy to ravulizumab or eculizumab for the treatment of extravascular hemolysis (EVH) in adults with paroxysmal nocturnal hemoglobinuria (PNH) (1).

Limitations of Use

VOYDEYA has not been shown to be effective as monotherapy and should only be prescribed as an add-on to ravulizumab or eculizumab.

2 DOSAGE AND ADMINISTRATION

- Start 150 mg three times a day orally, with or without food. Depending on clinical response, can increase to 200 mg three times a day.
- See Full Prescribing Information for instructions on dosage and administration (2.1, 2.2).

3 DOSAGE FORMS AND STRENGTHS

Tablets: 50 mg and 100 mg (3)

4 CONTRAINDICATIONS

Initiation in patients with unresolved serious infection caused by encapsulated bacteria (4).

5 WARNINGS AND PRECAUTIONS

- Hepatic Enzyme Increases: Assess liver enzymes before treatment initiation and periodically during treatment. Consider treatment interruption or discontinuation if elevations are clinically significant or if the patient becomes symptomatic (5.3).
- Hyperlipidemia: Monitor serum lipids periodically during treatment and initiate cholesterol-lowering medication if indicated (5.4).

6 ADVERSE REACTIONS

Most frequent adverse reaction (incidence ≥10%) was headache (6).

To report SUSPECTED ADVERSE REACTIONS, contact Alexion Pharmaceuticals, Inc. at 1-844-259-6783 or FDA at 1-800-FDA-1088 or www.fda.gov/medwatch.

7 DRUG INTERACTIONS

- BCRP substrates: Monitor patients more frequently for adverse reactions and consider dose reduction of the BCRP substrate drug. For rosuvastatin, the dose should not exceed 10 mg once daily (7.1).
- P-gp substrates: Dose adjustment might be necessary for P-gp substrates where minimal concentration changes may lead to serious adverse reactions (7.2).

8 USE IN SPECIFIC POPULATIONS

Hepatic Impairment: Avoid use in patients with severe hepatic impairment (Child-Pugh C) (8.6).

FULL PRESCRIBING INFORMATION

WARNING: SERIOUS INFECTIONS CAUSED BY ENCAPSULATED BACTERIA

VOYDEYA, a complement inhibitor, increases the risk of serious infections, especially those caused by encapsulated bacteria, such as Neisseria meningitidis, Streptococcus pneumoniae, and Haemophilus influenzae type B [see Warnings and Precautions (5.1)]. Life-threatening and fatal infections with encapsulated bacteria have occurred in patients treated with complement inhibitors. These infections may become rapidly life-threatening or fatal if not recognized and treated early.

- Complete or update vaccination for encapsulated bacteria specifically, Neisseria meningitidis and Streptococcus pneumoniae at least 2 weeks prior to the first dose of VOYDEYA, unless the risks of delaying therapy with VOYDEYA outweigh the risk of developing a serious infection. Comply with the most current Advisory Committee on Immunization Practices (ACIP) recommendations for vaccinations against encapsulated bacteria in patients receiving a complement inhibitor. See Warnings and Precautions (5.1) for additional guidance on the management of the risk of serious infections caused by encapsulated bacteria.
- Patients receiving VOYDEYA are at increased risk for invasive disease caused by encapsulated bacteria, even if they develop antibodies following vaccination. Monitor patients for early signs and symptoms of serious infections and evaluate immediately if infection is suspected.

Because of the risk of serious infections caused by encapsulated bacteria, VOYDEYA is available only through a restricted program under a Risk Evaluation and Mitigation Strategy (REMS) called the VOYDEYA REMS [see Warnings and Precautions (5.2)].

1 INDICATIONS AND USAGE

VOYDEYA is indicated as add-on therapy to ravulizumab or eculizumab for the treatment of extravascular hemolysis (EVH) in adults with paroxysmal nocturnal hemoglobinuria (PNH).

Limitations of Use

VOYDEYA has not been shown to be effective as monotherapy and should only be prescribed as an add-on to ravulizumab or eculizumab.

2 DOSAGE AND ADMINISTRATION

2.1 Recommended Vaccination and Prophylaxis for Encapsulated Bacterial Infections

Vaccinate patients against encapsulated bacteria, including Neisseria meningitidis (serogroups A, C, W, Y, and B) and Streptococcus pneumoniae according to current ACIP recommendations at least 2 weeks prior to initiation of VOYDEYA.

If urgent VOYDEYA therapy is indicated in a patient who is not up to date with vaccines for Neisseria meningitidis and Streptococcus pneumoniae according to ACIP recommendations, provide the patient with antibacterial drug prophylaxis and administer these vaccines as soon as possible [see Warnings and Precautions (5.1)].

Healthcare professionals who prescribe VOYDEYA must enroll in the VOYDEYA REMS [see Warnings and Precautions (5.2)].

2.2 Recommended Dosage

Starting Dose:

The recommended dosage of VOYDEYA is 150 mg three times a day administered orally.

VOYDEYA can be taken with or without food.

Dose Adjustment:

The dose can be increased to 200 mg three times a day if the patient's hemoglobin (Hgb) level has not increased by greater than 2 g/dL after 4 weeks of therapy, if the patient required a transfusion during the previous 4 weeks, or to achieve an appropriate Hgb response based on clinical judgement.

Missed Doses

A patient who misses a dose of VOYDEYA should take it as soon as they remember unless it is within 3 hours prior to their next dose, in which case the patient should skip the missed dose and take VOYDEYA at the next regularly scheduled time. Patients should not take two or more doses of VOYDEYA at the same time.

3 DOSAGE FORMS AND STRENGTHS

Tablets:

- 50 mg, white to off-white, round, film-coated, printed with "DCN" above "50" debossed on one side, plain on the other side.
- 100 mg, white to off-white, round film-coated, printed with "DCN" above "100" debossed on one side, plain on the other side.

4 CONTRAINDICATIONS

VOYDEYA is contraindicated for initiation in patients with unresolved serious infection caused by encapsulated bacteria, including Neisseria meningitidis, Streptococcus pneumoniae, or Haemophilus influenzae type B [see Warnings and Precautions (5.1)].

5 WARNINGS AND PRECAUTIONS

5.1 Serious Infections Caused by Encapsulated Bacteria

VOYDEYA, a complement inhibitor, increases a patient's susceptibility to serious, life-threatening, or fatal infections caused by encapsulated bacteria including Neisseria meningitidis (caused by any serogroup, including non-groupable strains), Streptococcus pneumoniae, and Haemophilus influenzae type B. Life-threatening and fatal infections with encapsulated bacteria have occurred in both vaccinated and unvaccinated patients treated with complement inhibitors. The initiation of VOYDEYA treatment is contraindicated in patients with unresolved serious infections caused by encapsulated bacteria.

Complete or update vaccination against encapsulated bacteria, specifically Neisseria meningitidis and Streptococcus pneumoniae at least 2 weeks prior to administration of the first dose of VOYDEYA, according to the current ACIP recommendations for patients receiving a complement inhibitor. Revaccinate patients in accordance with ACIP recommendations considering the duration of therapy with VOYDEYA. Note that ACIP recommends an administration schedule in patients receiving complement inhibitors that differs from the administration schedule in the vaccine prescribing information. If urgent VOYDEYA therapy is indicated in a patient who is not up to date with vaccines against encapsulated bacteria according to ACIP recommendations, provide the patient with antibacterial drug prophylaxis and administer these vaccines as soon as possible. Various durations and regimens of antibacterial drug prophylaxis have been considered, but the optimal durations and drug regimens for prophylaxis and their efficacy have not been studied in unvaccinated or vaccinated patients receiving complement inhibitors, including VOYDEYA. The benefits and risks of treatment with VOYDEYA, as well as the benefits and risks of antibacterial drug prophylaxis in unvaccinated or vaccinated patients, must be considered against the known risks for serious infections caused by encapsulated bacteria.

Vaccination does not eliminate the risk of serious encapsulated bacterial infections, despite development of antibodies following vaccination. Closely monitor patients for early signs and symptoms of serious infection and evaluate patients immediately if an infection is suspected. Inform patients of these signs and symptoms and instruct patients to seek immediate medical care if these signs and symptoms occur. Promptly treat known infections. Serious infection may become rapidly life-threatening or fatal if not recognized and treated early. Consider interruption of VOYDEYA in patients who are undergoing treatment for serious infections.

VOYDEYA is available only through a restricted program under a REMS [see Warnings and Precautions (5.2)].

5.2 VOYDEYA REMS

VOYDEYA is available only through a restricted program under a REMS called VOYDEYA REMS, because of the risk of serious infections caused by encapsulated bacteria [see Warnings and Precautions (5.1)].

Notable requirements of the VOYDEYA REMS include the following:

- Prescribers must enroll in the REMS.
- Prescribers must counsel patients about the risk of serious infections caused by encapsulated bacteria.
- Prescribers must provide patients with the REMS educational materials.
- Prescribers must assess patient vaccination status for vaccines against encapsulated bacteria and vaccinate if needed according to current ACIP recommendations two weeks prior to the first dose of VOYDEYA.
- Prescribers must provide a prescription for antibacterial drug prophylaxis if treatment must be started urgently, and the patient is not up to date with vaccines against encapsulated bacteria according to current ACIP recommendations at least two weeks prior to the first dose of VOYDEYA.
- Pharmacies that dispense VOYDEYA must be certified in the VOYDEYA REMS and must verify prescribers are certified.
- Patients must receive counseling from the prescriber about the need to receive vaccinations against encapsulated bacteria per ACIP recommendations, the need to take antibiotics as directed by the prescriber, and the early signs and symptoms of serious infections.
- Patients must be instructed to carry the Patient Safety Card with them at all times during treatment and for 1 week following the last dose of VOYDEYA.

Further information is available by telephone: 1-888-765-4747 or online at www.VoydeyaREMS.com.

5.3 Hepatic Enzyme Increases

Hepatic enzyme elevations have been observed in patients treated with VOYDEYA [see Adverse Reactions (6.1)]. Fourteen percent of patients receiving VOYDEYA in Study ALXN2040-PNH-301 had elevations in serum alanine aminotransferase (ALT). ALT elevations > 3 × the upper limit of normal (ULN) and ≤ 5 × ULN occurred in 9% of VOYDEYA-treated patients, and ALT elevations > 5 × ULN and ≤ 10 × ULN occurred in 5% of VOYDEYA-treated patients.

Assess liver enzyme test results prior to the initiation of VOYDEYA and periodically during treatment. Consider treatment interruption or discontinuation if elevations are clinically significant or if the patient becomes symptomatic. VOYDEYA has not been studied in patients with severe hepatic impairment [see Use in Specific Populations (8.7)].

5.4 Monitoring of PNH Manifestations After VOYDEYA Discontinuation

After discontinuing treatment with VOYDEYA, closely monitor patients for at least 2 weeks after the last dose for signs and symptoms of hemolysis. If discontinuation of VOYDEYA is necessary, continue background treatment with ravulizumab or eculizumab or consider alternative therapy if necessary. The signs and symptoms of hemolysis may include a sudden decrease in hemoglobin or fatigue.

If hemolysis occurs after discontinuation of VOYDEYA, consider restarting treatment with VOYDEYA if appropriate.

5.5 Hyperlipidemia

VOYDEYA increases total cholesterol and LDL-cholesterol.

Of the 50 VOYDEYA-treated patients who had a normal total cholesterol level at baseline in Study ALXN2040-PNH-301, 30% developed Grade 1 hypercholesterolemia. Of the 6 VOYDEYA treated patients who had Grade 1 hypercholesterolemia at baseline in Study ALXN2040-PNH-301, 1 patient experienced increased total cholesterol that worsened to Grade 2. Of the 54 VOYDEYA-treated patients who had LDL-cholesterol ≤130 mg/dL at baseline in Study ALXN2040-PNH-301, 13% developed LDL-cholesterol >130-160 mg/dL and 9% developed LDL-cholesterol >160-190 mg/dL.

Some patients required cholesterol-lowering medications.

Monitor serum lipid parameters periodically during treatment with VOYDEYA and initiate cholesterol lowering medication, if indicated.

6 ADVERSE REACTIONS

The following clinically significant adverse reactions are discussed in greater detail in other sections of the labeling:

- Serious Infections Caused by Encapsulated Bacteria [see Warnings and Precautions (5.1)]
- Hepatic Enzyme Increases [see Warnings and Precautions (5.3)]
- Hyperlipidemia [see Warnings and Precautions (5.4)]

6.1 Clinical Trials Experience

Because clinical trials are conducted under widely varying conditions, adverse reaction rates observed in the clinical trials of a drug cannot be directly compared to rates in the clinical trials of another drug and may not reflect the rates observed in practice.

The safety of VOYDEYA was evaluated in 86 adults with PNH in Study ALXN2040-PNH-301 [see Clinical Studies (14)]. Study ALXN2040-PNH-301 enrolled adults with PNH with clinically significant EVH who had been treated with a stable dose of ravulizumab or eculizumab for at least the previous 6 months. Patients were randomly assigned 2:1 to receive double-blind VOYDEYA 150 mg (n=57) or placebo (n=29) orally three times a day in addition to ravulizumab or eculizumab for 12 weeks. Patients received either US-approved or non-US-approved ravulizumab or eculizumab in the trial. Among patients who were randomized to receive VOYDEYA, 84% were exposed for at least 12 weeks.

Serious adverse reactions were reported in 5% of patients who received VOYDEYA and included pancreatitis, cholecystitis, and blood bilirubin increased. No specific serious adverse reaction was reported in more than 1 patient treated with VOYDEYA.

Permanent discontinuation of VOYDEYA due to an adverse reaction occurred in 5% of patients and included 1 patient with blood bilirubin increase and pancreatitis, 1 patient with hepatic enzyme increased, and 1 patient with ALT increased and aspartate aminotransferase increased. Dosage reduction due to an adverse reaction occurred in 1 patient and the adverse reaction was COVID-19.

Among the 57 patients treated with VOYDEYA in Study ALXN2040-PNH-301, the most common adverse reaction (≥10%) was headache.

Table 1 describes adverse reactions reported in ≥5% of patients treated with VOYDEYA and greater than placebo in the randomized, controlled period of Study ALXN2040-PNH-301.

Table 1 Adverse Reactions Reported in ≥5% of VOYDEYA-Treated Patients with PNH and Greater than Placebo
Adverse Reactions [Common Toxicity Criteria Adverse Events (CTCAE)] | VOYDEYA (with ravulizumab or eculizumab) N = 57 | Placebo (ravulizumab or eculizumab only) N = 29
Adverse Reactions [Common Toxicity Criteria Adverse Events (CTCAE)] | n (%) | n (%)
Headache | 6 (11) | 3 (10)
Vomiting [Represents a composite of multiple, related adverse reactions] | 4 (7) | 0 (0)
Pyrexia | 4 (7) | 0 (0)
Alanine aminotransferase increased | 3 (5) | 1 (3)
Hypertension | 3 (5) | 1 (3)
Pain in extremity | 3 (5) | 0 (0)

Clinically relevant adverse reactions in <5% of patients include increased serum triglycerides.

7 DRUG INTERACTIONS

7.1 BCRP Substrates

Danicopan is a Breast Cancer Resistance Protein (BCRP) inhibitor. Concomitant use of VOYDEYA with a BCRP substrate increases the plasma concentrations of the BCRP substrate [see Clinical Pharmacology (12.3)], which may increase the risk for adverse reactions associated with the BCRP substrate. If used together, monitor patients more frequently for adverse reactions associated with the BCRP substrate, and consider dose reduction of the BCRP substrate according to its prescribing information.

Rosuvastatin

Danicopan significantly increased rosuvastatin exposure. The dose of rosuvastatin should not exceed 10 mg once daily when concomitantly used with VOYDEYA [see Clinical Pharmacology (12.3)].

7.2 P-gp Substrates

Danicopan is an inhibitor of P-glycoprotein (P-gp). Concomitant administration of VOYDEYA with a P-gp substrate may increase the plasma concentration of the P-gp substrate. Dose adjustment might be necessary for P-gp substrates where minimal concentration changes may lead to serious adverse reactions [see Clinical Pharmacology (12.3)].

8 USE IN SPECIFIC POPULATIONS

8.1 Pregnancy

Risk Summary

There are no available data on VOYDEYA use in pregnant individuals to evaluate for a drug-associated risk of major birth defects, miscarriage or adverse maternal or fetal outcomes. There are risks to the mother and fetus associated with untreated PNH in pregnancy (see Clinical Considerations). The use of VOYDEYA in pregnant women or women planning to become pregnant may be considered following an assessment of the risks and benefits.

In animal reproduction studies, oral administration of danicopan to pregnant New Zealand White (NZW) rabbits and Wistar Hans (WH) rats during organogenesis at exposures 18 or 25-times, respectively, above the human exposure at the maximum recommended human dose (MRHD) of 200 mg three times a day (based on AUC) resulted in no adverse developmental effects (see Data).

The estimated background risk of major birth defects and miscarriage for the indicated population is unknown. All pregnancies have a background risk of birth defect, loss, or other adverse outcomes. In the U.S. general population, the estimated background risk of major birth defects and miscarriage in clinically recognized pregnancies is 2-4% and 15-20%, respectively.

Clinical Considerations

Disease-Associated Maternal and/or Fetal/Neonatal Risk

PNH in pregnancy is associated with adverse maternal outcomes, including worsening cytopenias, thrombotic events, infections, bleeding, miscarriages, and increased maternal mortality, and adverse fetal outcomes, including fetal death and premature delivery.

Data

Animal Data

There were no effects on early embryonic development and fetal development in NZW rabbits (where danicopan is pharmacodynamically active) up to a mean maternal systemic exposure 18-times the exposure at the MRHD (based on AUC) or during post-natal development up to a mean maternal systemic exposure 9-times the exposure at the MRHD (based on AUC). In WH rats (where danicopan lacks pharmacodynamic activity), there were no effects on embryo-fetal development up to a mean maternal exposure 25-times the exposure at the MRHD (based on AUC).

8.2 Lactation

Risk Summary

There are no data on the presence of danicopan in human milk, the effects on the breastfed child, or the effect on milk production. Danicopan is present in animal milk. When a drug is present in animal milk, it is likely that the drug will be present in human milk.

Because of the potential for serious adverse reactions in the breastfed child, including serious infections with encapsulated bacteria and liver enzyme increases, advise patients not to breastfeed during treatment with VOYDEYA, and for 3-days after the last dose.

Data

Animal Data

Danicopan was excreted into the milk of lactating rabbits following oral administration from lactation day 4 to lactation day 10, with mean milk concentrations at approximately 2 hours following dose administration 5- and 3.5-times higher than the mean maternal plasma concentrations at 50 and 250 mg/kg/day, respectively. Mean milk concentrations in dams were 19- and 43-times higher than the systemic exposure at the MRHD (based on rabbit concentration at 2 hours vs. human Cmax).

8.4 Pediatric Use

Safety and effectiveness of VOYDEYA for the treatment of PNH in pediatric patients have not been established.

8.5 Geriatric Use

There were 22 patients 65 years of age and older in the clinical studies for PNH [see Clinical Studies (14)]. Of the total number of VOYDEYA-treated patients in these studies, 16 (28.1%) were 65 years of age and older, and 7 (12.3%) were 75 years of age and older. Clinical studies of VOYDEYA did not include sufficient numbers of subjects aged 65 years and over to determine whether they respond differently from younger subjects.

8.6 Hepatic Impairment

No dose adjustment is required in patients with mild to moderate hepatic impairment (Child-Pugh Class A and B). Studies have not been conducted in patients with severe hepatic impairment, therefore, avoid use of VOYDEYA in this patient population [see Warnings and Precautions (5.3)].

10 OVERDOSAGE

Serum ALT elevations occurred after treatment cessation without a taper in 2 healthy subjects who received danicopan 500 mg and 800 mg twice a day. These abnormal ALT findings were transient, with no evidence of hepatic function abnormality and resolved spontaneously. In case of overdose, elevations in liver enzymes may occur. General supportive measures are recommended. It is not known if VOYDEYA can be removed by dialysis.

11 DESCRIPTION

Danicopan is a small molecule complement Factor D inhibitor. Its chemical name is (2S,4R)-1-{[3-acetyl-5-(2-methylpyrimidin-5-yl)-1H-indazol-1-yl] acetyl}-N-(6-bromopyridin-2-yl)-4-fluoropyrrolidine-2-carboxamide. Its molecular formula is C26H23BrFN7O3 and its molecular weight is 580.4. Danicopan has the following structural formula:

Danicopan is a white/off-white to pale yellow powder. In aqueous solutions, danicopan is considered slightly soluble at pH 1.2 and insoluble from pH 4 to pH 7.

Danicopan tablets are available as white to off-white, round, film-coated, immediate release tablets in strengths of 50 mg and 100 mg, intended for oral administration. Each tablet contains the following inactive ingredients: colloidal silicon dioxide, croscarmellose sodium, hypromellose acetate succinate, lactose monohydrate, magnesium stearate, microcrystalline cellulose, and sodium lauryl sulfate. The tablet coating components are polyethylene glycol, polyvinyl alcohol, talc, and titanium dioxide.

12 CLINICAL PHARMACOLOGY

12.1 Mechanism of Action

Danicopan binds reversibly to complement Factor D and selectively inhibits the alternative complement pathway. Danicopan prevents the cleavage of complement Factor B into the Ba and Bb fragments which are required for the formation of the alternative pathway (AP) complement component C3 convertase (C3bBb), the generation of downstream effectors including C3 fragment opsonization, and the amplification of the terminal pathway.

In PNH, intravascular hemolysis (IVH) is mediated by the terminal membrane attack complex (MAC), while extravascular hemolysis (EVH) is facilitated by C3 fragment opsonization. Danicopan acts proximally in the alternative pathway of the complement cascade to control preferentially C3 fragment-mediated EVH, while co-administered ravulizumab or eculizumab is anticipated to maintain control over MAC-mediated IVH.

12.2 Pharmacodynamics

Danicopan inhibits the AP of the complement system, as demonstrated by the decrease in ex vivo serum AP activity and in vivo plasma Bb concentration. Danicopan also reduces complement C3 fragment deposition on circulating red blood cells (RBCs) in PNH patients.

In patients with PNH undergoing treatment with ravulizumab or eculizumab, co-administration of VOYDEYA from 150 mg three times a day to 200 mg three times a day inhibited AP activity by >90%. Additionally, plasma Bb levels decreased by about 50% and the fraction of circulating PNH RBCs with measured C3 fragment deposition decreased by over 50%.

Cardiac Electrophysiology

At a single-dose of 1200 mg that results in approximately 2 times the peak concentration achieved following 200 mg three times a day, VOYDEYA does not prolong the QTc interval to any clinically relevant extent.

12.3 Pharmacokinetics

At the recommended dosages of 150 or 200 mg three times a day, the median systemic exposure of danicopan at steady state has a maximum plasma concentration (Cmax,ss) of 535 or 665 ng/mL, respectively, and has an area under the plasma drug concentration time curve (AUC24,ss) of 8180 or 10200 ng × h/mL, respectively.

Danicopan exposures at steady state generally increase in a dose-proportional manner from 150 mg three times a day to 200 mg three times a day. Danicopan systemic exposure reaches steady state in approximately 2 days. An approximately 2-fold accumulation of danicopan exposure is expected at steady state following thrice daily dosing compared to a single dose.

Absorption

The median time to maximum drug concentration (Tmax) is 3.7 hours following oral administration of 150 mg danicopan in patients with PNH.

Effect of Food

When the danicopan tablet was administered with a high-fat meal, danicopan AUC and Cmax were approximately 25%, and 93% higher, respectively, compared to the fasted state. Median time to maximum drug concentration (Tmax) was comparable when danicopan was administered in the fed or fasted state at approximately 3.0 and 2.5 hours, respectively.

Distribution

Plasma protein binding of danicopan is 91.5% to 94.3%. Danicopan is mainly distributed in plasma with a whole blood to plasma distribution ratio of 0.545. The apparent volume of distribution for a 75 kg person was 395 L.

Elimination

The mean half-life (t½) is 7.9 hours. The mean apparent clearance of danicopan is 63 L/h.

Metabolism

Danicopan is extensively metabolized (96%) via oxidation, reduction, and hydrolysis pathways, with amide hydrolysis being the major pathway of elimination. Metabolism by CYP-mediated pathways is minimal.

Excretion

After a single oral administration of 150 mg [^14C]-danicopan in humans, 69% of total radioactivity (danicopan plus metabolites) was excreted in feces and 25% was excreted in urine. Unchanged danicopan accounted for 3.57% and 0.48% of the dose excreted in feces and urine, respectively.

Specific Populations

No clinically significant differences in the pharmacokinetics of danicopan were observed based on sex, age (16.9 to 82 years), or race (Caucasians and Asians) based on population pharmacokinetic (PK) assessment.

Renal Impairment

Following oral administration of danicopan 200 mg in subjects with severe renal impairment (eGFR < 30 mL/min/1.73 m^2), the extent of danicopan exposure (AUC0-inf) increased by 52% as compared to subjects with normal renal function. There was no clinically meaningful change in Cmax and Tmax.

Hepatic Impairment

Danicopan Cmax decreased by 27% and AUC0-inf decreased by 8% in subjects with moderate hepatic impairment (Child-Pugh B). Studies have not been conducted in patients with severe hepatic impairment (Child-Pugh Class C).

Drug Interaction Studies

Clinical Studies

Effect of Danicopan on the Pharmacokinetics of Other Drugs:

Dedicated clinical drug interaction studies showed no clinically significant drug interactions with danicopan as an inhibitor or inducer of CYP2B6 (bupropion), CYP2C9 (warfarin), CYP2C19 (omeprazole), CYP3A4 (midazolam), and UGT1A1 and UGT2B7 (mycophenolic acid).

BCRP Substrates

Co-administration of a single oral dose of rosuvastatin 20 mg with danicopan dosed to steady state (200 mg three times a day for 4 days) resulted in increased rosuvastatin Cmax and AUC0-inf by 3.3-fold and 2.2-fold, respectively.

P-gp Substrates

Co-administration of a single oral dose of fexofenadine 180 mg with danicopan dosed to steady state (150 mg three times a day for 4 days) resulted in increased fexofenadine Cmax and AUC0-inf by 1.4-fold and 1.6-fold, respectively.

Co-administration of a single oral dose of tacrolimus 2 mg with danicopan dosed to steady state (200 mg three times a day for 5 days) resulted in increased tacrolimus Cmax and AUC0-inf by 1.1-fold and 1.5-fold, respectively.

Effect of Other Drugs on the Pharmacokinetics of Danicopan:

No clinically significant drug interactions were observed for danicopan as a victim when co-administered with antacid drugs (calcium carbonate, aluminum/magnesium hydroxide/simethicone) or a proton pump inhibitor (omeprazole).

In Vitro Studies

Non-CYP based metabolism is the predominant clearance pathway for danicopan. The minimal contribution of CYP metabolism in human hepatocytes is suggestive of a very low likelihood of danicopan as a victim of CYP-based drug-drug interactions.

Danicopan is a substrate of P-gp, but not a substrate of BCRP, Organic Anion Transporting Polypeptide 1B1 (OATP1B1), or OATP1B3. Danicopan is not an inducer of CYP1A2, CYP2B6 or CYP2C9.

Danicopan is an inhibitor of BCRP and P-gp, but not an inhibitor of transporters OATP1B1, OATP1B3, Organic Anion Transporter (OAT)1, OAT3, Organic Cation Transporter 2 (OCT2), or Multidrug And Toxin Extrusion 1 and 2K (MATE1 and MATE2-K).

13 NONCLINICAL TOXICOLOGY

13.1 Carcinogenesis, Mutagenesis, Impairment of Fertility

Carcinogenesis

Danicopan was not carcinogenic in the 6-month carcinogenicity study in the TgRasH2 mouse model. Danicopan was not carcinogenic in the 2-year rat carcinogenicity study at exposures 15- to 23-times the exposure at the MRHD (based on AUC).

Mutagenesis

Danicopan was not genotoxic in the Ames bacterial reverse mutation assay, in vitro micronucleus assay in human peripheral blood lymphocytes, or in the in vivo micronucleus assay in rats.

Impairment of Fertility

In a rabbit study, reductions in male and female fertility and copulation/conception indices were observed at mean exposures 13-times the exposure at the MRHD (based on AUC).

13.2 Animal Toxicology and/or Pharmacology

Ocular phototoxicity was observed in pigmented rats at systemic exposures 15-times and 28-times the exposure at the MRHD (based on AUC and Cmax, respectively). As danicopan is expected to accumulate in the eye, a risk of developing ocular phototoxicity cannot be excluded in patients on long-term danicopan therapy who are exposed to unprotected ultraviolet radiation for extended periods of time. The clinical significance of these findings is unknown.

14 CLINICAL STUDIES

Paroxysmal Nocturnal Hemoglobinuria (PNH)

The efficacy of VOYDEYA in adults with PNH and clinically significant EVH was assessed in a multiple-region, randomized, double-blind, placebo-controlled study (ALXN2040-PNH-301; NCT04469465). Clinically significant EVH was defined by anemia (hemoglobin [Hgb] ≤ 9.5 g/dL) with absolute reticulocyte count ≥ 120 × 10^9/L with or without transfusion support. The study enrolled patients with PNH who had been treated with a stable dose of ravulizumab or eculizumab for at least the previous 6 months.

VOYDEYA was administered orally at 150 mg three times a day, escalated to 200 mg three times a day depending on the clinical response.

Patients were vaccinated against meningococcal infection prior to or at the time of initiating treatment with VOYDEYA if vaccination status within 3 years could not be verified.

Patients were randomized to VOYDEYA or placebo in a 2:1 ratio for 12 weeks in addition to background ravulizumab or eculizumab treatment. After Week 12, all patients received VOYDEYA in combination with their background ravulizumab or eculizumab treatment up to Week 24. After Week 24, patients could enter a long-term extension period and continue to receive VOYDEYA with background ravulizumab or eculizumab.

Efficacy was based on the change in Hgb level from Baseline to Week 12. Other efficacy measures included the proportion of patients with Hgb increase of ≥ 2 g/dL at Week 12 in the absence of transfusions, the proportion of patients with transfusion avoidance through Week 12, the change from Baseline in Functional Assessment of Chronic Illness Therapy (FACIT)-Fatigue scores at Week 12, and change from Baseline in absolute reticulocyte count at Week 12. Transfusion avoidance was considered as achieved only by the patients who did not receive a transfusion and did not meet the protocol specified guidelines for transfusion from Baseline through Week 12.

A pre-specified interim analysis was performed when 63 participants reached the end (either completed or discontinued) of Week 12.

Baseline demographic and disease history characteristics were generally balanced between treatment groups.

Table 2 presents the baseline characteristics of the patients with PNH enrolled in the study.

Table 2 Baseline Characteristics in PNH Study (ALXN2040-PNH-301)
Parameter | Statistics | VOYDEYA (Add-on to ravulizumab or eculizumab) N = 42 | Placebo (Add-on to ravulizumab or eculizumab) N = 21
Age (years) | Mean (SD) | 55 (16) | 53 (14)
 | Median | 58 | 53
 | Min, max | 25, 80 | 29, 75
Sex | n (%)
Male |  | 19 (45.2) | 7 (33.3)
Female |  | 23 (54.8) | 14 (66.7)
Race | n (%)
American Indian or Alaska Native |  | 1 (2.4) | 0
Asian |  | 18 (42.9) | 7 (33.3)
Black or African American |  | 1 (2.4) | 0
White |  | 19 (45.2) | 9 (42.9)
Other |  | 1 (2.4) | 0
Unknown |  | 0 | 1 (4.8)
Not Reported |  | 2 (4.8) | 4 (19.0)
Ethnicity | n (%)
Hispanic or Latino |  | 4 (9.5) | 0
Not Hispanic or Latino |  | 34 (81.0) | 17 (81.0)
Not reported |  | 4 (9.5) | 4 (19.0)
Hemoglobin level (g/dL) | Mean (SD) | 7.7 (0.9) | 7.7 (1.0)
Reticulocyte count (10^9/L) | N | 42 | 20
 | Mean (SD) | 236 (91) | 241 (120)
Number of patients with pRBC/whole blood transfusions within 24 weeks prior to first dose | n (%) | 38 (90) | 17 (81)
pRBC/whole blood Transfusions within 24 weeks prior to first dose | Mean (SD) | 2.5 (2.2) | 2.6 (2.1)
LDH (U/L) | N | 42 | 20
LDH (U/L) | Mean (SD) | 299 (106) | 278 (68)
FACIT-Fatigue score [Fatigue-related symptoms and impacts were assessed using a patient reported outcome instrument, FACIT-Fatigue (score range from 0 to 52 with higher scores indicating less fatigue).] | Mean (SD) | 33 (11) | 34 (11)
Background treatment with: | n (%)
Ravulizumab |  | 27 (64.3) | 10 (47.6)
Eculizumab |  | 15 (35.7) | 11 (52.4)
Abbreviations: FACIT = Functional Assessment of Chronic Illness Therapy; LDH = lactate dehydrogenase; N = number of patients; pRBC = packed red blood cell; SD = standard deviation

Efficacy was established based on demonstration of superiority of VOYDEYA in combination with ravulizumab or eculizumab compared to placebo in combination with ravulizumab or eculizumab in all efficacy measures with statistically significant results (Table 3).

Table 3 Efficacy Results for Patients with PNH (Study ALXN2040-PNH-301)
 | VOYDEYA (Add-on to ravulizumab or eculizumab) (N = 42) | Placebo (Add-on to ravulizumab or eculizumab) (N = 21)
Change in Hemoglobin Level [The model included the fixed, categorical effects of treatment group, study visit, and study visit-by-treatment group interaction, as well as the fixed, continuous covariate of baseline value and the randomization stratification factor of transfusion history. An unstructured covariance matrix was used to model the within-patient errors.]
Mean change from Baseline to Week 12 (g/dL) | 2.9 | 0.5
Treatment difference | 2.4 (95% CI: 1.7, 3.2)
P-value | 0.0007 [Statistical significance of the treatment group difference was evaluated via a re-randomization test method. The p-value for the re-randomization test was calculated as the number of re-randomized treatment group differences that were more extreme than the treatment group difference calculated under the actual randomization divided by the total number of simulated re-randomizations.]
Proportion of Patients with Hemoglobin Increase of ≥ 2 g/dL in the Absence of Transfusion [The proportions were compared between treatment groups using the Cochrane-Mantel-Haenszel (CMH) test stratified by randomization stratification factors of transfusion history and screening Hgb level. The p-value was from the stratified CMH test.]
At Week 12 (%) | 59.5 | 0
Treatment difference | 46.9 (95% CI: 29.2, 64.7)
P-value | < 0.0001
Proportion of Patients with Transfusion Avoidance
Through 12-Week Treatment Period (%) | 83.3 | 38.1
Treatment difference | 41.7 (95% CI: 22.7, 60.8)
P-value | 0.0004
Change in FACIT-Fatigue Score [The model included the fixed, categorical effects of treatment group, study visit, and study visit-by-treatment group interaction, as well as the fixed, continuous covariate of baseline value and the randomization stratification factors of transfusion history and screening Hgb level. An unstructured covariance matrix was used to model the within-patient errors. Fatigue-related symptoms and impacts were assessed using a patient reported outcome instrument, FACIT-Fatigue (score range from 0 to 52 with higher scores indicating less fatigue).]
Mean change from Baseline to Week 12 | 8.0 | 1.9
Treatment difference | 6.1 (95% CI: 2.3, 9.9)
P-value | 0.002 [The p-value was for the difference of LS mean from the mixed models for repeated measures (MMRM).]
Change in Absolute Reticulocyte Count
Mean change from Baseline to Week 12 (10^9/L) | -84 | 4
Treatment difference | -87 (95% CI: -118, -57)
P-value | < 0.0001
Abbreviations: CI = confidence interval; FACIT = Functional Assessment of Chronic Illness Therapy

16 HOW SUPPLIED/STORAGE AND HANDLING

VOYDEYA (danicopan) tablets are available in the doses and packages listed in Table 4.

Table 4 VOYDEYA Tablet Presentations
Dose | Tablet Strength | Film-Coated Tablet Markings | Tablet Color/Shape | Pack Size | NDC Code
Each carton contains two high density polyethylene bottles with desiccant and child resistant seal, with 180 tablets per carton:
150 mg | 50 mg | Debossed on one side with "DCN 50" | White to off-white, round film-coated tablets | One bottle with 90 × 50 mg per tablet (25682-040-90) One bottle with 90 × 100 mg per tablet (25682-043-90) | 25682-046-92
150 mg | 100 mg | Debossed on one side with "DCN 100" | White to off-white, round film-coated tablets | One bottle with 90 × 50 mg per tablet (25682-040-90) One bottle with 90 × 100 mg per tablet (25682-043-90) | 25682-046-92
200 mg | 100 mg | Debossed on one side with "DCN 100" | White to off-white, round film-coated tablets | Two bottles with 90 tablets per bottle: 90 × 100 mg per tablet (25682-043-90) | 25682-043-92
Each carton contains four 7-day blister cards with 168 tablets per carton:
150 mg | 50 mg | Debossed on one side with "DCN 50" | White to off-white, round film-coated tablets | Four blister cards with 42 tablets per card: 21 × 50 mg per tablet and 21 × 100 mg per tablet (25682-049-42) | 25682-049-04
150 mg | 100 mg | Debossed on one side with "DCN 100" | White to off-white, round film-coated tablets | Four blister cards with 42 tablets per card: 21 × 50 mg per tablet and 21 × 100 mg per tablet (25682-049-42) | 25682-049-04
200 mg | 100 mg | Debossed on one side with "DCN 100" | White to off-white, round film-coated tablets | Four blister cards with 42 tablets per card: 42 × 100 mg per tablet (25682-043-42) | 25682-043-04

STORAGE AND HANDLING

Store and dispense in the original container at 20°C to 25°C (68°F to 77°F) with excursions permitted between 15°C and 30°C (59°F and 86°F) [see USP controlled room temperature].

17 PATIENT COUNSELING INFORMATION

Advise the patient to read the FDA-approved patient labeling (Medication Guide).

Serious Infections Caused by Encapsulated Bacteria

Advise patients of the risk of serious infection. Inform patients of the need to complete or update their vaccinations against encapsulated bacteria at least 2 weeks prior to receiving the first dose of VOYDEYA or receive antibacterial drug prophylaxis if VOYDEYA treatment must be initiated immediately and they have not previously been vaccinated. Inform patients of the requirement to be revaccinated according to ACIP recommendations for encapsulated bacteria while on VOYDEYA therapy [see Warnings and Precautions (5.1)].

Inform patients that vaccination may not prevent serious infection and to seek immediate medical attention if the following signs or symptoms occur [see Warnings and Precautions (5.1)]:

- fever with or without chills
- fever and a rash
- fever with chest pain and cough
- fever with breathlessness/fast breathing
- fever with high heart rate
- headache with nausea or vomiting
- headache and a fever
- headache with a stiff neck or stiff back
- confusion
- body aches with flu-like symptoms
- clammy skin
- eyes sensitive to light

Inform patients that they will be given a Patient Safety Card for VOYDEYA that they should carry with them at all times during and for 1 week following treatment with VOYDEYA. This card describes symptoms which, if experienced, should prompt the patient to seek immediate medical evaluation.

VOYDEYA REMS

VOYDEYA is available only through a restricted program called VOYDEYA REMS [see Warnings and Precautions (5.2)].

Inform the patient of the following notable requirements:

- Patients must receive counseling about the risk of serious infections caused by encapsulated bacteria.
- Patients must receive written educational materials about this risk.
- Patients must be instructed to carry the Patient Safety Card with them at all times during treatment and for 1 week following the last dose of VOYDEYA.
- Patients must be instructed to complete or update vaccines against encapsulated bacteria per ACIP recommendations as directed by the prescriber prior to treatment with VOYDEYA.
- Patients must receive antibiotics as directed by the prescriber if they are not up to date on vaccinations against encapsulated bacteria and have to start VOYDEYA right away.

Importance of Adherence to Dosing Schedule

Inform patients with PNH of the importance of taking VOYDEYA as prescribed to minimize the risk of hemolysis.

Discontinuation

Inform patients with PNH that they may develop serious hemolysis due to PNH if VOYDEYA is discontinued and that they should be monitored by their healthcare providers for at least 2 weeks following discontinuation of VOYDEYA.

Inform patients who discontinue VOYDEYA to keep the Patient Safety Card with them for 1 week after the last dose of VOYDEYA. The increased risk of serious infection may continue for a few days after the last dose of VOYDEYA.

Hepatic Enzyme Elevations

Inform patients that elevation in liver enzymes have occurred in patients treated with VOYDEYA, and liver tests will be obtained before and during VOYDEYA treatment [see Warnings and Precautions (5.3)].

Hyperlipidemia

Inform patients that VOYDEYA may increase their cholesterol and that monitoring of these parameters will be needed periodically during treatment [see Warnings and Precautions (5.4)].

Manufactured for:

Alexion Pharmaceuticals, Inc.
121 Seaport Boulevard
Boston, MA 02210 USA

This product, or its use, may be covered by one or more US patents, including US Patent No. 9,796,741 B2 in addition to others including patents pending.

VOYDEYA is a trademark of Alexion Pharmaceuticals, Inc.

© 2024 Alexion Pharmaceuticals, Inc.

MEDICATION GUIDE
VOYDEYA™(voi-day-uh)
(danicopan)
tablets, for oral use

What is the most important information I should know about VOYDEYA?

VOYDEYA is a medicine that affects your immune system. VOYDEYA may lower the ability of your immune system to fight infections.

- VOYDEYA increases your chance of getting serious infections caused by encapsulated bacteria, including Neisseria meningitidis, Streptococcus pneumoniae, and Haemophilus influenzae type B. These serious infections may quickly become life-threatening and cause death if not recognized and treated early.
  - You must complete or be up to date with the vaccines against Neisseria meningitidis and Streptococcus pneumoniae at least 2 weeks before your first dose of VOYDEYA.
  - If you have not completed your vaccinations and VOYDEYA must be started right away, you should receive the required vaccinations as soon as possible.
  - If you have not been vaccinated at least 2 weeks before your first VOYDEYA dose, and treatment with VOYDEYA must be started right away, you should also receive antibiotics to take for as long as your healthcare provider tells you.
  - If you have been vaccinated against these bacteria in the past, you might need additional vaccinations before starting VOYDEYA. Your healthcare provider will decide if you need additional vaccinations.
  - Vaccines do not prevent all infections caused by encapsulated bacteria. Call your healthcare provider or get emergency medical care right away if you have any of these signs and symptoms of a serious infection:

- fever with or without chills
- fever and a rash
- fever with chest pain and cough
- fever with breathlessness/fast breathing
- fever with high heart rate
- headache with nausea or vomiting

- headache and a fever
- headache with a stiff neck or stiff back
- confusion
- body aches with flu-like symptoms
- clammy skin
- eyes sensitive to light

Your healthcare provider will give you a Patient Safety Card about the risk of serious infections. Carry it with you at all times during treatment and for 1 week after your last VOYDEYA dose. Your risk of serious infections may continue for a few days after your last dose of VOYDEYA. If you get any of the symptoms listed on this card you should get medical help right away. It is important to show this card to any healthcare provider who treats you. This will help them diagnose and treat you quickly.

- VOYDEYA is only available through a program called the VOYDEYA REMS. Before you can take VOYDEYA, your healthcare provider must:
  - enroll in the VOYDEYA REMS.
  - counsel you about the risk of serious infections caused by certain bacteria.
  - give you information about the symptoms of serious infections.
  - make sure that you are vaccinated against serious infections caused by encapsulated bacteria and that you receive antibiotics if you need to start VOYDEYA right away and you are not up to date on your vaccinations.
  - give you a Patient Safety Card about your risk of serious infections, as discussed above.

For more information about side effects, see "What are the possible side effects of VOYDEYA?"

What is VOYDEYA?

VOYDEYA is a prescription medicine used along with ravulizumab or eculizumab to treat breakdown of red blood cells that takes place outside of blood vessels (extravascular hemolysis), in adults with paroxysmal nocturnal hemoglobinuria (PNH).
It is not known if VOYDEYA is safe and effective in children.

Who should not take VOYDEYA?

Do not take VOYDEYA if you have a serious infection caused by encapsulated bacteria, including Neisseria meningitidis, Streptococcus pneumoniae, or Haemophilus influenzae type B when you are starting VOYDEYA treatment.

Before taking VOYDEYA, tell your healthcare provider about all of your medical conditions, including if you:

- have an infection or fever
- have liver problems
- are pregnant or plan to become pregnant. It is not known if VOYDEYA will harm your unborn baby.
- are breastfeeding or plan to breastfeed. It is not known if VOYDEYA passes into your breast milk. Do not breastfeed during treatment with VOYDEYA and for 3 days after the last dose.

Tell your healthcare provider about all the medicines you take, including prescription and over-the-counter medicines, vitamins, and herbal supplements. VOYDEYA may affect the way other medicines work.

Know the medicines you take and the vaccines you receive. Keep a list of them to show your healthcare provider and pharmacist when you get a new medicine.

How should I take VOYDEYA?

- Take VOYDEYA exactly as your healthcare provider tells you to take it.
- Depending on the dose prescribed, the number of tablets is as follows:
  - 150 mg dose: take 1 tablet of 100 mg and 1 tablet of 50 mg together 3 times a day.
  - 200 mg dose: take 2 tablets of 100 mg 3 times a day.
- Do not change the dose or stop taking VOYDEYA unless your healthcare provider tells you.
- Take VOYDEYA by mouth.
- Take VOYDEYA with or without food.
- Take your doses of VOYDEYA around the same time every day.
- If you forget to take your scheduled dose, take it as soon as you remember. If it is within 3 hours of your next dose, skip the missed dose and take your next scheduled dose at your regularly scheduled time. Do not take 2 doses of VOYDEYA at the same time.
- If you take too much VOYDEYA, call your healthcare provider or go to the nearest emergency room right away.
- If you stop taking VOYDEYA, your healthcare provider will need to monitor you closely for at least 2 weeks after the last dose. Stopping treatment with VOYDEYA may cause a breakdown of red blood cells due to PNH.
  Symptoms or problems that can happen due to breakdown of red blood cells include:
  - decreased hemoglobin level in your blood
  - tiredness

What are the possible side effects of VOYDEYA?

VOYDEYA may cause side effects, including:

- See "What is the most important information I should know about VOYDEYA?"
- Increased liver enzyme levels. Your healthcare provider will do blood tests to check your liver enzyme levels before and during treatment with VOYDEYA. Your healthcare provider may temporarily or permanently stop treatment with VOYDEYA if you develop increased liver enzyme levels.
- Increased cholesterol. VOYDEYA may increase your cholesterol. Your healthcare provider will do blood tests to check your cholesterol during treatment with VOYDEYA.

The most common side effect of VOYDEYA is headache.

Tell your healthcare provider about any side effect that bothers you or that does not go away.

These are not all of the possible side effects of VOYDEYA.

Call your doctor for medical advice about side effects. You may report side effects to FDA at 1-800-FDA-1088.

How should I store VOYDEYA?

- Store VOYDEYA in the original container between 68°F and 77°F (20°C and 25°C).
- Keep VOYDEYA and all medicines out of the reach of children.

General information about the safe and effective use of VOYDEYA.

Medicines are sometimes prescribed for purposes other than those listed in a Medication Guide. Do not use VOYDEYA for a condition for which it was not prescribed. Do not give VOYDEYA to other people, even if they have the same symptoms you have. It may harm them. You can ask your pharmacist or healthcare provider for information about VOYDEYA that is written for health professionals.

What are the ingredients in VOYDEYA?

Active ingredient: danicopan

Inactive ingredients: colloidal silicon dioxide, croscarmellose sodium, hypromellose acetate succinate, lactose monohydrate, magnesium stearate, microcrystalline cellulose, and sodium lauryl sulfate.

The film coatings contain the following inactive ingredients: polyethylene glycol, polyvinyl alcohol, talc, and titanium dioxide.

Manufactured for: Alexion Pharmaceuticals, Inc., 121 Seaport Boulevard, Boston, MA 02210 USA
VOYDEYA is a trademark of Alexion Pharmaceuticals, Inc.
© 2024 Alexion Pharmaceuticals, Inc
For more information, go to www.VOYDEYA.com or call 1-888-765-4747.

This Medication Guide has been approved by the U.S. Food and Drug Administration.

Issued: 03/2024

PRINCIPAL DISPLAY PANEL - 100 mg Tablet Blister Pack Carton - 043-04

NDC 25682-043-04
Rx only

Voydeya™
(danicopan) tablets

Dispense with enclosed Medication Guide.

100 mg per tablet

Take two 100 mg tablets three times a day
(200 mg dose three times a day)

Four 7-day blister cards with 42 tablets per card (168 tablets)

PRINCIPAL DISPLAY PANEL - 100 mg Tablet Bottle Carton - 043-92

NDC 25682-043-92
Rx only

Voydeya™
(danicopan) tablets

Dispense with enclosed Medication Guide.

100 mg

180 tablets
90 x 100 mg tablets per bottle

PRINCIPAL DISPLAY PANEL - Kit Carton - 049

NDC 25682-049-04
Rx only

Voydeya™
(danicopan) tablets

Dispense with enclosed Medication Guide.

50 mg per tablet
and
100 mg per tablet

Take one 100 mg tablet and one 50 mg tablet
three times a day
(150 mg dose three times a day)

Four 7-day blister cards with 42 tablets per card (168 tablets)
21 x 50 mg per tablet
21 x 100 mg per tablet

PRINCIPAL DISPLAY PANEL - Kit Carton - 046

NDC 25682-046-92
Rx only

Voydeya™
(danicopan) tablets

Dispense with enclosed Medication Guide.

50 mg
and
100 mg

Take one 100 mg tablet and one 50 mg tablet
three times a day
(150 mg dose three times a day)

180 tablets
90 x 50 mg tablets per bottle
90 x 100 mg tablets per bottle